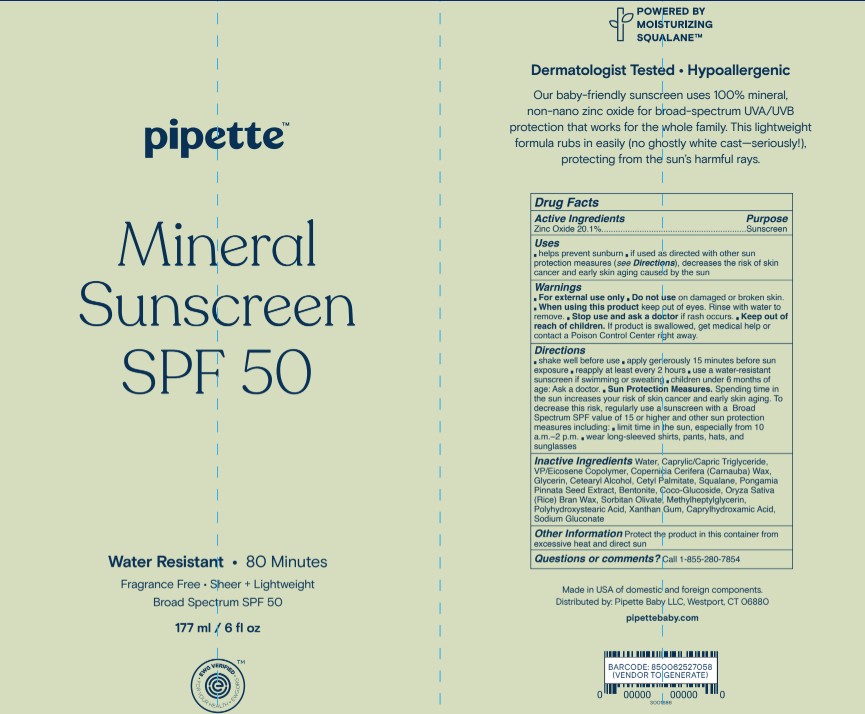 DRUG LABEL: Pipette Mineral Sunscreen Broad Spectrum SPF 50
NDC: 84723-001 | Form: LOTION
Manufacturer: Pipette LLC
Category: otc | Type: HUMAN OTC DRUG LABEL
Date: 20250507

ACTIVE INGREDIENTS: ZINC OXIDE 201 mg/1 mL
INACTIVE INGREDIENTS: WATER; CAPRYLIC/CAPRIC TRIGLYCERIDE; GLYCERIN; SQUALANE; CETEARYL ALCOHOL; SORBITAN OLIVATE; CETYL PALMITATE; COCO GLUCOSIDE; COPERNICIA CERIFERA (CARNAUBA) WAX; BENTONITE; POLYHYDROXYSTEARIC ACID (2300 MW); XANTHAN GUM; CAPRYLHYDROXAMIC ACID; SODIUM GLUCONATE

Pipette Mineral Sunscreen Broad Spectrum SPF 50 Water Resistant 80 Minutes

Active Ingredients

Zinc Oxide 20.1%

Purpose

Sunscreen

Uses

Helps prevent sunburn

if used as directed with other sun protection measures(see directions), decreases the risk of skkin cancer and early signs of aging caused by the sun.

Warnings

For external use only

Do not use

on damaged of broken skin

When using this product

keep out of eyes. Rinse with water to remove

Stop use and ask

a doctor if rash occurs

Keep out of reach of children

If product is swallowed, get medical help or contact a Poison Control Center right away.

Directions

- Shake well before use
- Apply generously 15 minutes before sun exposure
- reapply at least every 2 hours
- use a water-resistant sunscreen if swimming or sweating
- children under 6 months of age:ask a doctor.
- Sun Protection Measures Spending time in the sun increases your risk of skin cancer and early skin aging. To decrease this risk, regularyly use a sunscreen with a Broad Spectrum value of SPF 15 or higher and other sun protection measures including
- Limit time in the sun, especially from 10 a.m.- 2 p.m.
- wear long-sleeved shiirts, pants, hats and sunglasses

Inactive ingredients

Water, Caprylic/Capric Triglyceride,VP/Eicosene Copolymer, Copernicia Cerifera (Carnauba) Wax,Glycerin, Cetearyl Alcohol, Cetyl Palmitate, Squalane, PongamiaPinnata Seed Extract, Bentonite, Coco-Glucoside, Oryza Sativa(Rice) Bran Wax, Sorbitan Olivate, Methylheptylglycerin,Polyhydroxystearic Acid, Xanthan Gum, Caprylhydroxamic Acid, Sodium Gluconate

Other Information

Protect the product in this container fromexcessive heat and direct sun

Questions or comments?

Call 1-855-280-7854